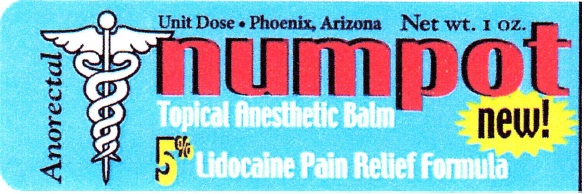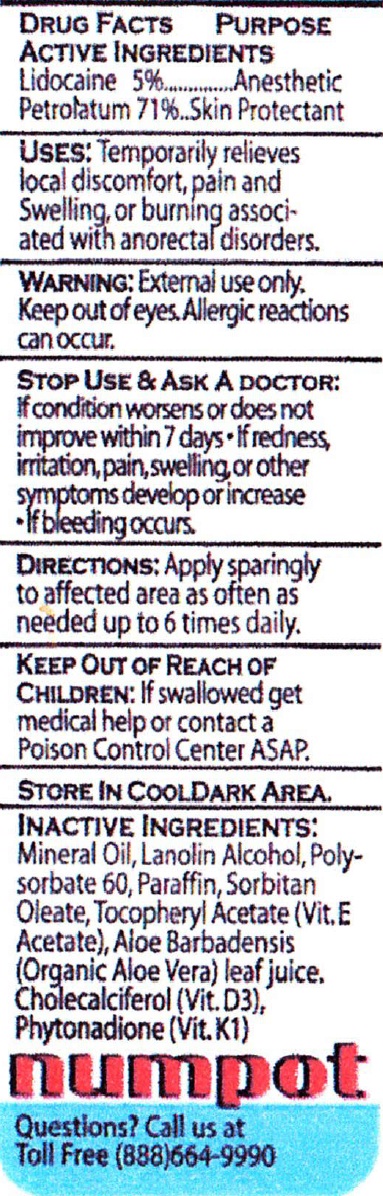 DRUG LABEL: Numpot Topical Anesthetic
NDC: 67194-018 | Form: OINTMENT
Manufacturer: Unit Dose, Ltd.
Category: otc | Type: HUMAN OTC DRUG LABEL
Date: 20231019

ACTIVE INGREDIENTS: LIDOCAINE 50 mg/1 g; PETROLATUM 710 mg/1 g
INACTIVE INGREDIENTS: MINERAL OIL; LANOLIN ALCOHOLS; POLYSORBATE 60; PARAFFIN; SORBITAN MONOOLEATE; .ALPHA.-TOCOPHEROL ACETATE; ALOE VERA LEAF; CHOLECALCIFEROL; PHYTONADIONE

Numpot Topical Anesthetic Balm

ACTIVE INGREDIENTS

Lidocaine 5%

Petrolatum 71%

PURPOSE

Anesthetic

Skin Protectant

USES:

Temporarily relieves local discomfort, pain and Swelling, or burning associated with anorectal disorders.

WARNING:

External use only. Keep out of eyes. Allergic reactions can occur.

STOP USE & ASK A DOCTOR:

If condition worsens or does not improve within 7 days

- If redness, irritation, pain, swelling or other symptoms develop or increase
- If bleeding occurs.

KEEP OUT OF REACH OF CHILDREN:

If swallowed get medical help or contact a Poison Control Center ASAP.

DIRECTIONS:

Apply sparingly to affected area as often as needed up to 6 times daily.

STORE IN COOL DARK AREA.

INACTIVE INGREDIENTS:

Mineral Oil, Lanolin Alcohol, Polysorbate 60, Paraffin, Sorbitan Oleate, Tocopheryl Acetate (Vit. E Acetate), Aloe Barbadensis (Organic Aloe Vera) leaf juice, Cholecalciferol (Vit. D3), Phytonadione (Vit. K1)

Questions?

Call us at Toll Free (888)664-9990